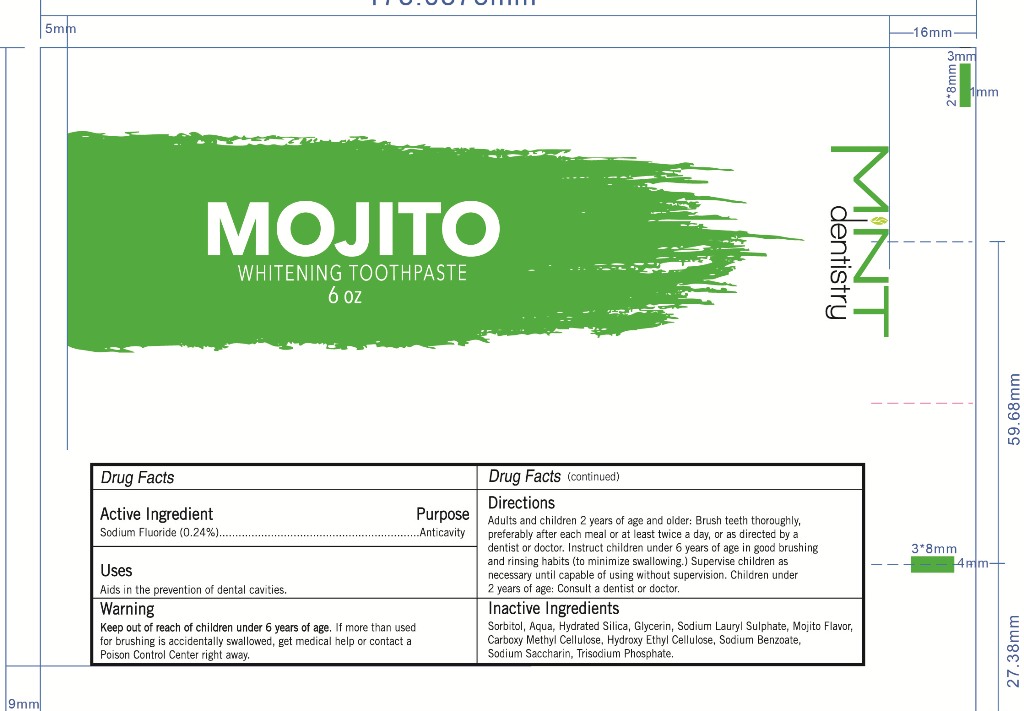 DRUG LABEL: mojito MINT dentistry
NDC: 73297-002 | Form: PASTE
Manufacturer: Jiangsu Shushi Biotechnology  Co., Ltd.
Category: otc | Type: HUMAN OTC DRUG LABEL
Date: 20190828

ACTIVE INGREDIENTS: SODIUM FLUORIDE 0.24 g/100 g
INACTIVE INGREDIENTS: SORBITOL; HYDRATED SILICA; HYDROXYETHYL CELLULOSE (40 MPA.S AT 2%); WATER; CARBOXYMETHYLCELLULOSE; GLYCERIN; SODIUM PHOSPHATE, TRIBASIC, ANHYDROUS; SODIUM BENZOATE; SODIUM LAURYL SULFATE; SACCHARIN SODIUM

73297-002 mojito MINT dentistry

Active ingredients

Sodium Fluoride 0.24%

Purpose

anticavity

Uses

aids in the prevention of dental vavities.

Warnings

Keep out of the reach of children under 6 years of age.if more than used for brushing is accidently swallowed,get medical help or contact a Poison Control Center right away.

Keep out of reach of children.

Directions

Adults and children 2years of age and older:Brush teeth thoroughly,preferably after each meal or at least twice a day,or as directed by a dentist or doctor.

Instruct Children under 6 years of age in good burshing and rinsing ahnbits(to mininize swallowing).supervise children as necessary until catlble of using without supervision.

Children under 2 years:Consult a dentist or doctor.

INACTIVE INGREDIENT

HYDRATED SILICA,HYDROXYETHYL CELLULOSE,WATER,CARBOXYMETHYLCELLULOSE,SACCHARIN SODIUM,SODIUM PHOSPHATE, TRIBASIC, ANHYDROUS.SODIUM BENZOATE,SODIUM LAURYL SULFATE,SORBITOL,GLYCERIN